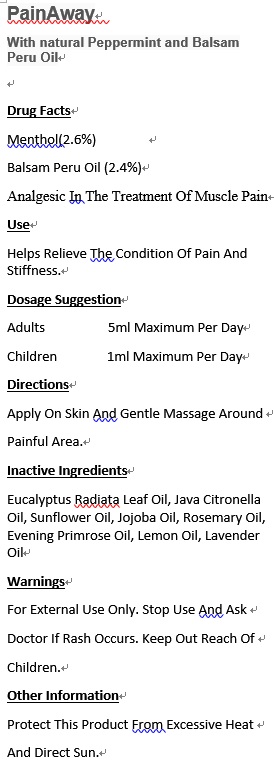 DRUG LABEL: Osteoarthritica Synergy
NDC: 70470-1123 | Form: OIL
Manufacturer: PHYTOPIA CO., LTD.
Category: otc | Type: HUMAN OTC DRUG LABEL
Date: 20161115

ACTIVE INGREDIENTS: MENTHOL 7 mg/50 mL
INACTIVE INGREDIENTS: ARNICA MONTANA; BALSAM PERU OIL; JUNIPER BERRY OIL; ORANGE OIL; OLIVE OIL; SUNFLOWER OIL; EVENING PRIMROSE OIL; ROSEMARY OIL; BLACK PEPPER OIL; TAMANU OIL

Drug Facts

menthol(2.6%)

Balsam Peru Oil (2.4%)

Analgesic in the treatment of muscle pain

Use

Helps relieve the condition of pain and stiffness.

Dosage Suggestion

Adults 5ml maximum per day

Children 1ml maximum per day

Directions

Apply on skin and gentle massage around painful area.

Inactive Ingredients

EUCALYPTUS RADIATA LEAF OIL, JAVA CITRONELLA OIL, SUNFLOWER OIL, JOJOBA OIL, ROSEMARY OIL, EVENING PRIMROSE OIL, LEMON OIL, LAVENDER OIL

Warnings

For external use only. Stop use and ask doctor if rash occurs. Keep out reach of children.

Other Information

Protect this product from excessive heat

and direct sun.

Warnings

For external use only. Stop use and ask doctor if rash occurs. Keep out reach of children.